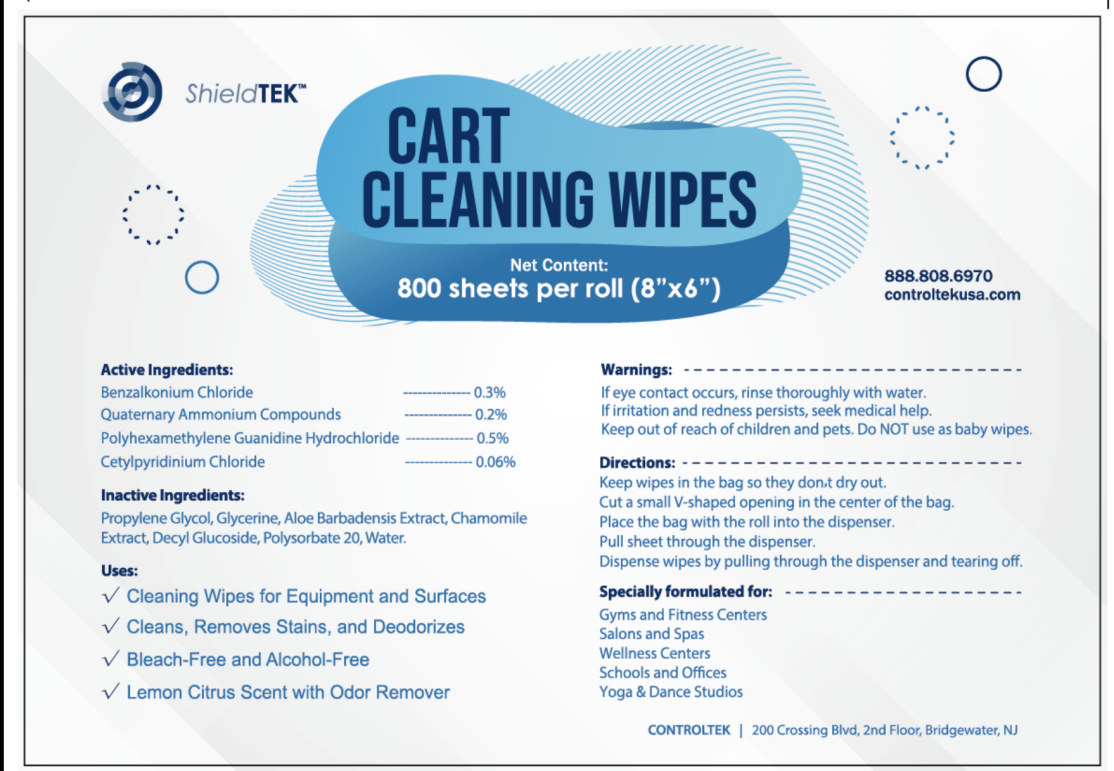 DRUG LABEL: CART CLEANING WIPES
NDC: 55415-010 | Form: CLOTH
Manufacturer: JIANGSU MEIFAN BIOTECHNOLOGY CO., LTD.
Category: otc | Type: HUMAN OTC DRUG LABEL
Date: 20201214

ACTIVE INGREDIENTS: POLYAMINOPROPYL BIGUANIDE 15.8 g/800 1; CETYLPYRIDINIUM CHLORIDE 1.9 g/800 1; BENZALKONIUM CHLORIDE 9.5 g/800 1; DIDECYLDIMONIUM CHLORIDE 6.3 g/800 1
INACTIVE INGREDIENTS: PROPYLENE GLYCOL; ALOE VERA LEAF; WATER; DECYL GLUCOSIDE; CHAMOMILE

DOSAGE AND ADMINISTRATION

Cut a small V-shaped opening in the center of the bag.

Place the bag with the roll into the dispenser.

Pull sheet through the dispenser.

Dispense wipes by pulling through the dispenser and tearing off.

INACTIVE INGREDIENT

Propylene Glycol, Aloe Bardadensis Extract, Chamomile Extract, Decyl Glucoside, Water

INDICATIONS AND USAGE

Shopping Carts

Gyms and Fitness Centers

Salons, Spas and Wellness Centers

Schools and Offices

Yoga & Dance Studios

HOW SUPPLIED

Store at room temperature in a cool, dry and ventilated place.

ACTIVE INGREDIENT

Benzalkonium Chloride 0.3%

Quaternary Ammonium Compounds 0.2%

Pholyhexamethylene Guanidine Hydrochloride 0.5%

Cetylpyridinium Chloride 0.06%

Keep out of reach of children and pets. Do not use as baby wipes.

uses

Cleaning Wipes for Equipment and Surfaces

Cleans, Removes Stains, and Deodorizes

Bleach-Free and Alcohol-Free

Lemon Citrus Scent with Odor Remover

WARNINGS

If eye contact occurs, rinse thoroughly with water.

If irritation and redness persist, seek medical help.

Keep out of reach of children and pets. Do not use as baby wipes.